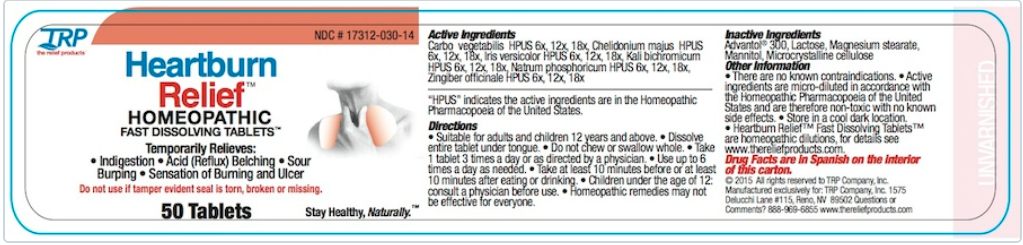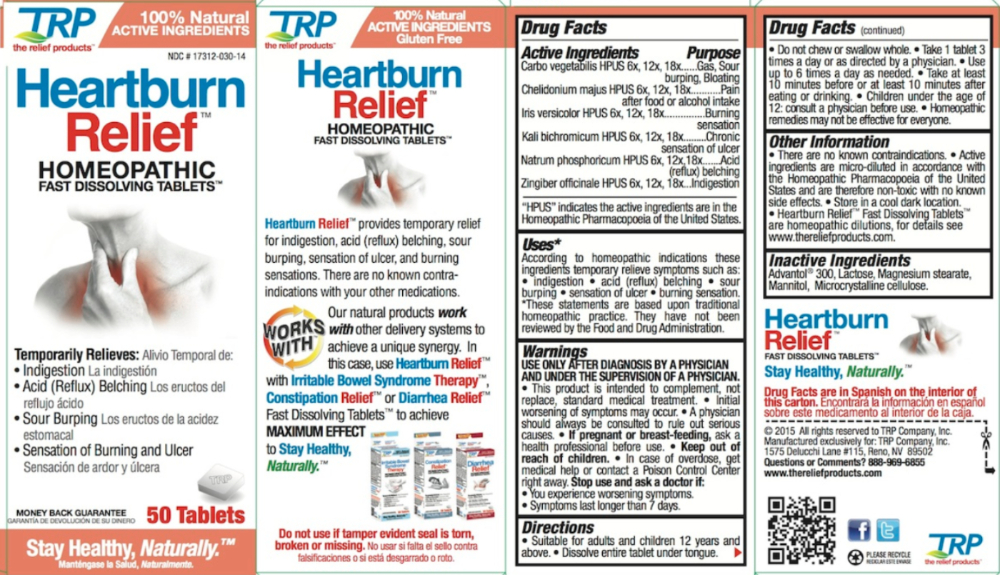 DRUG LABEL: Heartburn Relief
NDC: 17312-030 | Form: TABLET, ORALLY DISINTEGRATING
Manufacturer: TRP Company
Category: homeopathic | Type: HUMAN OTC DRUG LABEL
Date: 20251117

ACTIVE INGREDIENTS: ACTIVATED CHARCOAL 6 [hp_X]/1 1; POTASSIUM DICHROMATE 6 [hp_X]/1 1; CHELIDONIUM MAJUS 6 [hp_X]/1 1; SODIUM PHOSPHATE, DIBASIC, HEPTAHYDRATE 6 [hp_X]/1 1; GINGER 6 [hp_X]/1 1; IRIS VERSICOLOR ROOT 6 [hp_X]/1 1
INACTIVE INGREDIENTS: MANNITOL; SORBITOL; CROSPOVIDONE; CELLULOSE, MICROCRYSTALLINE; COPOVIDONE; SILICON DIOXIDE; LACTOSE; MAGNESIUM STEARATE

Heartburn Relief™

PURPOSE

Carbo vegetabilis HPUS - Gas, Sour burping, Bloating
Chelidonium majus HPUS - Pain after food or alcohol intake
Iris versicolor HPUS - Burning sensation
Kali bichromicum HPUS - Chronic sensation of ulcer
Natrum phosphoricum HPUS - Acid (reflux) belching
Zingiber officinale HPUS - Indigestion

Uses:*

According to homeopathic indications these ingredients temporarily relieve symptoms such as: • indigestion • acid (reflux) belching • sour burping • sensation of ulcer • burning sensation. * These statements are based upon traditional homeopathic practice. They have not been reviewed by the Food and Drug Administration.

Warnings:

USE ONLY AFTER DIAGNOSIS BY A PHYSICIAN AND UNDER THE SUPERVISION OF A PHYSICIAN.

- This product is intended to complement, not replace, standard medical treatment.
- Initial worsening of symptoms may occur.
- A physician should always be consulted to rule out serious causes.

PREGNANCY OR BREAST FEEDING

If pregnant or breast-feeding, ask a health professional before use.

WARNINGS

- In case of overdose, get medical help or contact a Poison Control Center right away.

Stop use and ask a doctor if:

- You experience worsening symptoms.
- If symptoms last longer than 7 days.

Directions

- Suitable for adults and children 12 years and above.
- Dissolve entire tablet under tongue.
- Do not chew or swallow whole.
- Take 1 tablet 3 times a day or as directed by a physician.
- Use up to 6 times a day as needed.
- Take at least 10 minutes before or at least 10 minutes after eating or drinking.
- Children under the age of 12: consult a physician before use.

Homeopathic remedies may not be effective for everyone.

Other information

- There are no known contraindications.
- Active ingredients are micro-diluted in accordance with the Homeopathic Pharmacopoeia of the United States and are therefore non-toxic with no known side effects.
- Store in a cool dark location.

Inactive Ingredients

Advantol® 300, Lactose, Magnesium Stearate, Mannitol, Microcrystalline Cellulose.

QUESTIONS

www.thereliefproducts.com, 1-888-969-6855

Active Ingredients

Carbo vegetabilis HPUS 6x, 12x, 18x
Chelidonium majus HPUS 6x, 12x, 18x
Iris versicolor HPUS 6x, 12x, 18x
Kali bichromicum HPUS 6x, 12x, 18x
Natrum phosphoricum HPUS 6x, 12x,18x
Zingiber officinale HPUS 6x, 12x, 18x

"HPUS" indicates the active ingredients are in the Homeopathic Pharmacopoeia of the United States.